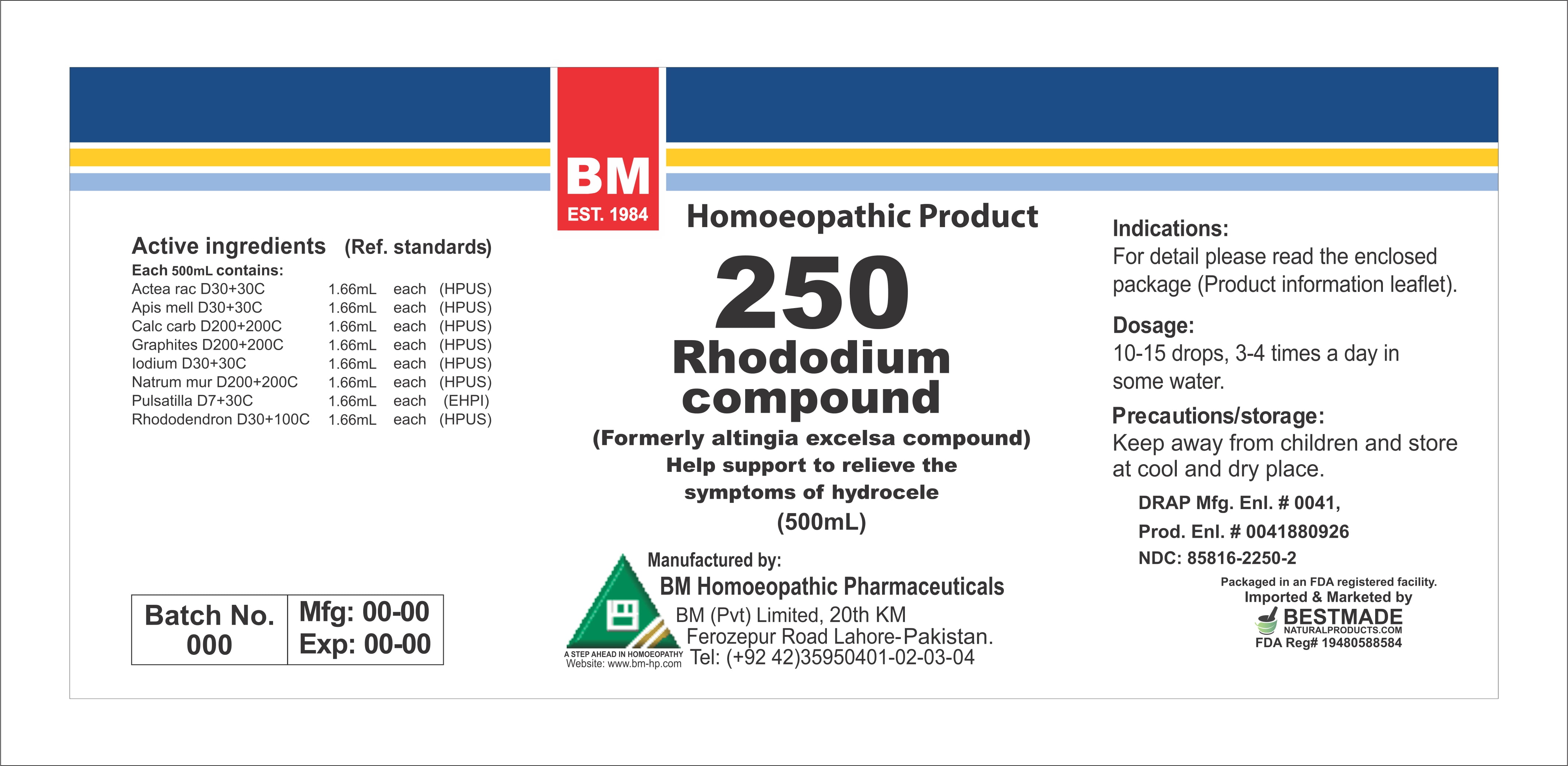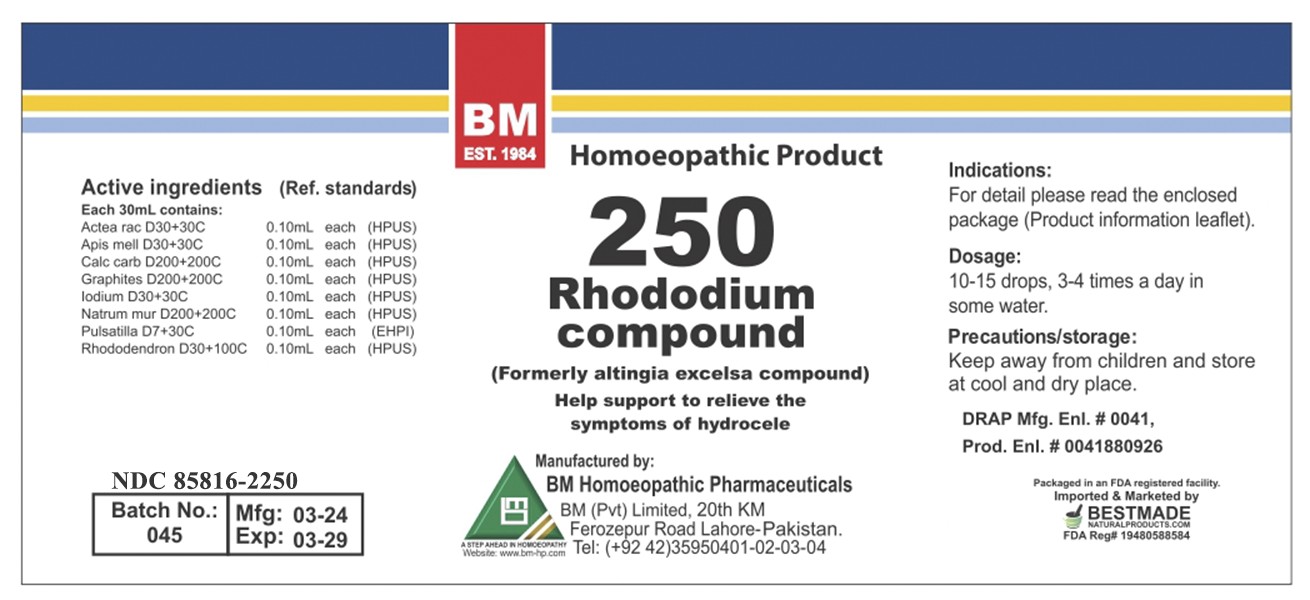 DRUG LABEL: RHODODIUM
NDC: 85816-2250 | Form: LIQUID
Manufacturer: BM Private Limited
Category: homeopathic | Type: HUMAN OTC DRUG LABEL
Date: 20260215

ACTIVE INGREDIENTS: OYSTER SHELL CALCIUM CARBONATE, CRUDE 200 [hp_X]/1 mL; BLACK COHOSH 30 [hp_X]/1 mL; GRAPHITE 200 [hp_X]/1 mL; RHODODENDRON FERRUGINEUM LEAF 30 [hp_X]/1 mL; SODIUM CHLORIDE 200 [hp_X]/1 mL; APIS MELLIFERA 30 [hp_X]/1 mL; IODINE 30 [hp_X]/1 mL; PULSATILLA PRATENSIS 7 [hp_X]/1 mL
INACTIVE INGREDIENTS: ALCOHOL 0.96 mL/1 mL

HOMEOPATHIC LIQUID RHODODIUM/ BM250

DOSAGE AND ADMINISTRATION

10-15 drops, 3-4 times a day in some water

ACTIVE INGREDIENT

actea racemosa, apis mell, calc carb, graphites, iodium, natrum mur, pulsatilla, rhododendron

INACTIVE INGREDIENT

ALCOHOL

INDICATIONS AND USAGE

For detail, please read the enclosed package (product information leaflet)

PURPOSE

For detail, please read the enclosed package (product information leaflet)

KEEP OUT OF REACH OF CHILDREN

Precautions/storage:
Keep away from children and store at cool and dry place.

WARNINGS

Precautions/storage:
Keep away from children and store at cool and dry place.

Package 1:

Package 2: